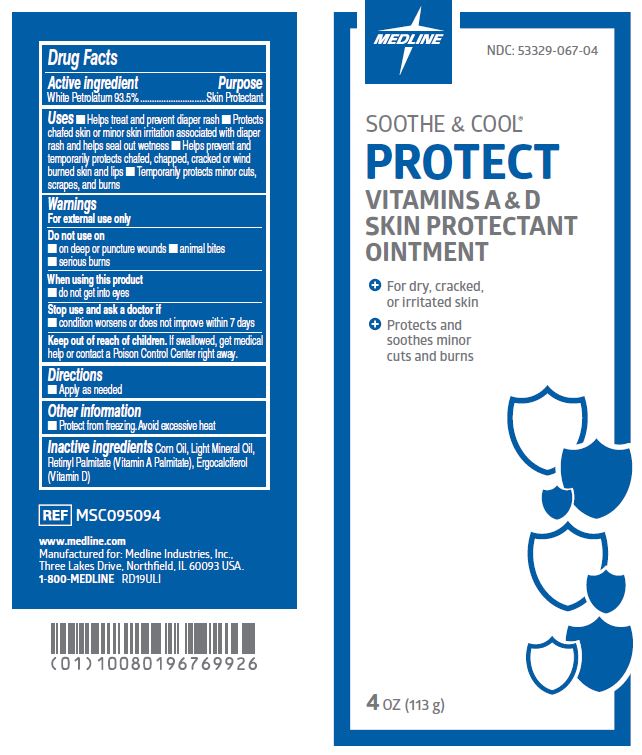 DRUG LABEL: Soothe and Cool
NDC: 53329-067 | Form: OINTMENT
Manufacturer: Medline Industries, LP
Category: otc | Type: HUMAN OTC DRUG LABEL
Date: 20221214

ACTIVE INGREDIENTS: PETROLATUM 935 mg/1 g
INACTIVE INGREDIENTS: ERGOCALCIFEROL; CORN OIL; LIGHT MINERAL OIL; VITAMIN A PALMITATE

067 Soothe and Cool Protect A&D

Active ingredient

White Petrolatum 93.5% w/w

Purpose

Skin Protectant

Uses

- helps treat and prevent diaper rash
- protects chafed skin or minor skin irritation associated with diaper rash and helps seal out wetness
- helps prevent and temporarily protects chafed, chapped, cracked or wind burned skin and lips
- temporarily protects minor cuts, scrapes, and burns

Warnings

For external use only

Do not use

- on deep or puncture wounds
- animal bites
- serious burns

When using this product

- do not get into eyes

Stop use and ask a doctor if

- condition worsens
- symptoms last for more than 7 days or clear up and occur again within a few days

Keep out of reach of children.

If swallowed, get medical help or contact a Poison Control Center right away.

Directions

- apply as needed

Other information

- Protect from freezeing. Avoid excessive heat.

Inactive ingredients

Corn Oil, Light Mineral Oil, Retinyl Palmitate (Vitamin A Palmitate), Ergocalciferol (Vitamin D)

Manufacturing Information

Manufactured for: Medline Industries, Inc.

Three Lakes Drive, Northfield, IL 60093 USA

Made in USA

www.medline.com

1-800-MEDLINE

REF: MSC095094

RD19ULI